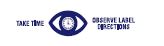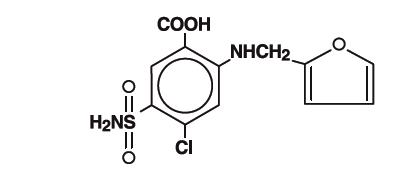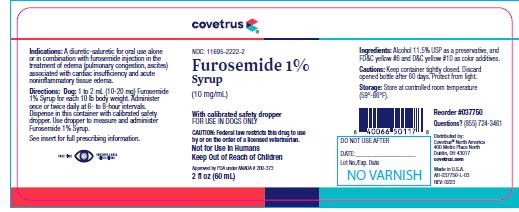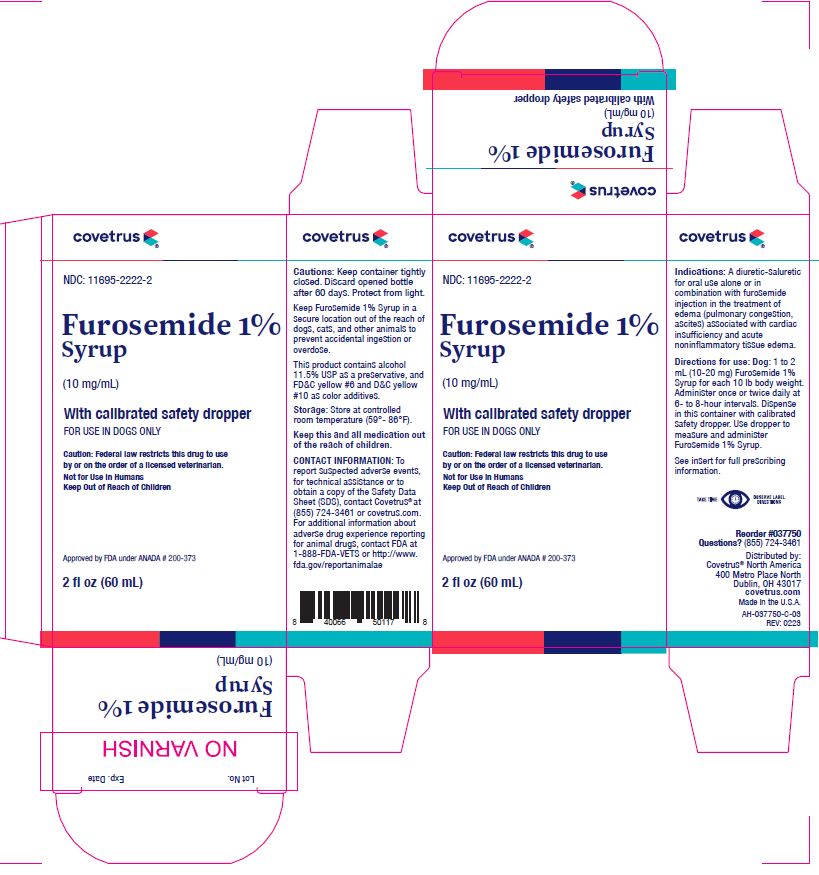 DRUG LABEL: Furosemide
NDC: 11695-2222 | Form: SYRUP
Manufacturer: Butler Animal health Supply, LLC dba Covetrus North America
Category: animal | Type: PRESCRIPTION ANIMAL DRUG LABEL
Date: 20240624

ACTIVE INGREDIENTS: FUROSEMIDE 10 mg/1 mL

Furosemide 1%
Syrup

VETERINARY INDICATIONS

(10 mg/mL)

With calibrated safety dropper
FOR USE IN DOGS ONLY

Caution:

Federal law restricts this drug to use by or on the order of a licensed veterinarian.

Not for Use in Humans
Keep Out of Reach of Children

Approved by FDA under ANADA # 200-373

VETERINARY INDICATIONS

A diuretic-saluretic for prompt relief of edema.

DESCRIPTION:

Furosemide Syrup 1% is a chemically distinct diuretic and saluretic pharmacodynamically characterized by the following:

1. A high degree of efficacy, low-inherent toxicity and a high therapeutic index.
2. A rapid onset of action of comparatively short duration. ^1,2
3. A pharmacologic action in the functional area of the nephron, i.e., proximal and distal tubules and the ascending limb of the loop Henle. ^2,4
4. A dose-response relationship and a ratio of minimum to maximum effective dose range greater than ten fold. ^1,2
5. It is administered orally. It is readily absorbed from the intestinal tract and well tolerated.

The CAS Registry Number is: 54-31-9.

This product contains alcohol 11.5% USP as a preservative, and FD&C Yellow #6 and D&C Yellow #10 as color additives.

Furosemide Syrup 1%, a diuretic, is an anthranilic acid derivative with the following structural formula:

Generic name: Furosemide (except in United Kingdom-frusemide). Chemical name: 4-chloro-N-furfuryl-5-sulfamoylanthranilic acid.

ACTIONS

The therapeutic efficacy of Furosemide Syrup 1 % is from the activity of the intact and unaltered molecule throughout the nephron, inhibiting the reabsorption of sodium not only in the proximal and distal tubule, but also in the ascending limb of the loop of Henle. The prompt onset of action is a result of the drug's rapid absorption and a poor lipid solubility. The low lipid solubility and a rapid renal excretion minimizes the possibility of lipid accumulation in tissues and organs or of crystalluria. Furosemide Syrup 1 % has no inhibitory effect on carbonic anhydrase or aldosterone activity in the distal tubule. The drug possesses diuretic activity in the presence of either acidosis or alkalosis. ^1-7

INDICATIONS

DOG

Furosemide Syrup 1% is an effective diuretic possessing a wide therapeutic range. Pharmacologically it promotes the rapid removal of abnormally retained extracellular fluids. The rationale for the efficacious use of diuretic therapy is determined by the clinical pathology producing the edema.

Furosemide Syrup 1% is indicated for the treatment of edema (pulmonary congestion, ascites) associated with cardiac insufficiency and acute noninflammatory tissue edema. The continued USB of heart stimulants, such as digitalis or its glycosides, is indicated in cases of edema involving cardiac insufficiency.

CONTRAINDICATIONS-PRECAUTIONS

Furosemide Syrup 1% is a highly effective diureticsaluretic which if given in excessive amounts may result in dehydration and electrolyte imbalance. Therefore, the dosage and schedule may have to be adjusted to the patients' needs. The animal should be observed for early signs of electrolyte imbalance, and corrective measures administered. Early signs of electrolyte imbalance are: Increased thirst, lethargy, drowsiness or restlessness, fatigue, oliguria, gastrointestinal disturbances and tachycardia. Special attention should be given to potassium levels.
Furosemide may lower serum calcium levels and cause tetany in rare cases of animals having an existing hypocalcemic tendency. ^10-14
Although diabetes mellitus is a rarely reported disease in animals, active or latent diabetes mellitus may on rare occasions be exacerbated by Furosemide Syrup 1%. While it has not been reported in animals, the use of high doses of salicylates, as in rheumatic diseases, in conjunction with Furosemide Syrup 1% may result in salicylate toxicity because of competition for renal excretory sites. Electrolyte balance should be monitored prior to surgery in patients receiving Furosemide Syrup 1%. Imbalances must be corrected by administration of suitable fluid therapy.
Furosemide Syrup 1% is contraindicated in anuria. Therapy should be discontinued in cases of progressive renal disease if increasing azotemia and oliguria occur during the treatment. Sudden alterations of fluid and electrolyte imbalance in an animal with cirrhosis may precipitate hepatic coma; therefore, observation during period of therapy is necessary. In hepatic coma and in states of electrolyte depletion, therapy should not be instituted until the basic condition is improved or corrected. Potassium supplementation may be necessary in cases routinely treated with potassium depleting steroids.

WARNINGS

Furosemide Syrup 1% is a highly effective diuretic and, as with any diuretic, if given in excessive amounts may lead to excessive diuresis that could result in electrolyte imbalance, dehydration and reduction of plasma volume, enhancing the risk of circulatory collapse, thrombosis, and embolism. Therefore, the animal should be observed for early signs of fluid depletion with electrolyte imbalance, and corrective measures administered. Excessive loss of potassium in patients receiving digitalis or its glycosides may precipitate digitalis toxicity. Caution should be exercised in animals administered potassium-depleting steroids.

It is important to correct potassium deficiency with dietary supplementation. Caution should be exercised in prescribing enteric-coated potassium tablets.

There have been several reports in human literature, published and unpublished, concerning nonspecific small-bowel lesions consisting of stenosis, with or without ulceration, associated with the administration of enteric-coated thiazides with potassium salts. These lesions may occur with enteric-coated potassium tablets alone or when they are used with non-enteric-coated thiazides, or certain other oral diuretics. These smallbowel lesions may have caused obstruction, hemorrhage, and perforation. Surgery was frequently required, and deaths have occurred. Available information tends to implicate enteric-coated potassium salts, although lesions of this type also occur spontaneously. Therefore, coated potassium-containing formulations should be administered only when indicated, and should be discontinued immediately if abdominal pain, distension, nausea, vomiting, or gastrointestinal bleeding occurs. Human patients with known sulfonamide sensitivity may show allergic reactions to Furosemide Syrup 1%; however, these reactions have not been reported in animals.

Sulfonamide diuretics have been reported to decrease arterial responsiveness to pressor amines and to enhance the effect of tubocurarine. Caution should be exercised in administering curare or its derivatives to patients undergoing therapy with Furosemide Syrup 1% and it is advisable to discontinue Furosemide Syrup 1% for one day prior to any elective surgery. Keep Furosemide Syrup 1% in a secure location out of the reach of dogs, cats, and other animals to prevent accidental ingestion or overdose.

CONTACT INFORMATION:

To report suspected adverse events, for technical assistance or to obtain a copy of the Safety Data Sheet (SDS), contact First Priority, Inc. at (800) 650-4899 or www.prioritycare.com. For additional information about adverse drug experience reporting for animal drugs, contact FDA at 1-888-FDA-VETS or http://www.fda.gov/reportanimalae

DOSAGE AND ADMINISTRATION

The usual dose of Furosemide Syrup 1 % is 1 to 2 mg/lb body weight (approximately 2.5 to 5 mg/kg). Administer once or twice daily at 6- to 8-hour intervals orally. A prompt diuresis usually ensues from the initial treatment. Diuresis may be initiated by the parenteral administration of furosemide injection and then maintained by oral administration.

The dosage should be adjusted to the individual's response. In severe edematous or refractory cases, the dose may be doubled or increased by increments of 1 mg/lb body weight. The established effective dose should be administered once or twice daily. The daily schedule of administration can be timed to control the period of micturition of the convenience of the client or veterinarian. Mobilization of the edema may be most efficiently and safely accomplished by utilizing an intermittent daily dosage schedule, i.e., every other day or 2 to 4 consecutive days weekly.

Diuretic therapy should be discontinued after reduction of the edema, or maintained after determining a carefully programmed dosage schedule to prevent recurrence of edema. For long-term treatment, the dose can generally be lowered after the edema has once been reduced.

Re-examination and consultations with client will enhance the establishment of a satisfactorily programmed dosage schedule. Clinical examination and serum BUN, CO^2 and electrolyte determinations should be performed during the early period of therapy and periodically thereafter, especially in refractory cases. Abnormalities should be corrected or the drug temporarily withdrawn.

DOSAGE

ORAL:

DOG-Syrup 1 %

One (1) to two (2) mL (10 to 20 mg furosemide) per 10 lb body weight (approximately 2.5 to 5 mg/kg).

Administered once or twice daily, permitting a 6- to 8-hour interval between treatments. In refractory or severe edematous cases, the dosage may be doubled or increased by increments of 1 mg/lb body weight as recommended in preceding paragraphs, "DOSAGE AND ADMINISTRATION."

HOW SUPPLIED Oral:

Furosemide Syrup 1% (10 mg/mL), available in 60 mL bottles with calibrated safety dropper.

TOXICOLOGY

Acute Toxicity:

The following table illustrates low acute toxicity of Furosemide Syrup 1% in three different species. (Two values indicated two different studies).

LD50 of Furosemide Syrup 1 percent in mg/kg body weight
SPECIES | ORAL | INTRAVENOUS
Mouse | 1050-1500 | 308
Rat | 2650-4600* | 680
Dog | >1000 and >4640 | >300 and >464

*NOTE: The lower oral LD50 value for the rat was obtained in a group of fasted animals; the higher figure is from a study performed on fed rats.

Toxic doses lead to convulsions, ataxia, paralysis and collapse. Animals surviving toxic doses may become dehydrated and depleted of electrolytes due to the massive diuresis and saluresis.

Chronic Toxicity:
Chronic toxicity studies with furosemide were done in a one-year study in rats and dogs. In a one-year study in rats, renal tubular degeneration occurred with all doses higher than 50 mg/kg. A six-month study in dogs revealed calcification and scarring of the renal parenchyma at all doses above 10 mg/kg.

Reproductive Studies:

Reproductive studies were conducted in mice, rats and rabbits. Only in rabbits administered high doses (equivalent to 10 to 25 times the recommended average dose of 2 mg/kg for dogs, horses and cattle) of furosemide during the second trimester did unexplained maternal deaths and abortions occur. Furosemide Syrup 1% should be used during pregnancy only if the potential benefit justifies the potential risk to the fetus. The effects of alcohol administered to pregnant Beagles at 3 and at 3.6 gms/kg/day throughout gestation suggests that alcohol may reduce the number of offspring per litter, the birth weight per pup and increase the incidence of stillbirths. There have been no studies conducted in pregnant dogs administered alcohol at levels found in Furosemide Syrup 1%.

REFERENCES

1. Timmerman RJ, Springman FR, Thomas RK: Evaluation of furosemide, a new diuretic agent. Curr Ther Res 6:88-94, 1964.
2. Muschaweck R, Hajdu P: The saluretic action of 4-Chloro-N-(2 furylmethyl)-5-sulfamyl-anthranilic acid. (Die salidiuretische Wirksamkeit der Chlor-N-(2- furylmethyl)-5-sulfamyl-anthranilsaure.) Arzneim Forsch 14:44-47, 1964.
3. Suki W, Rector FC Jr, Seldin DW: The site of action of furosemide and other sulfonamide diuretics in the dog. J Clin Invest 44:1458-1469, 1965.
4. Deetjen P: Micropuncture studies of the action of furosemide. (Mikropunktionsuntersuchungen zur Wirkung von Furosemid.) Pfluegers Arch 284:184-190, 1965.
5. Berman LB, Ebrahimi A: Experiences with furosemide in renal disease. Proc Soc Exp Biol Med 118:333-336, 1965.
6. Schmidt HAE: Animal experiments with S35 tagged Lasix® in canine and ovine. Internal report, Radiochemical Pharmacological Laboratory, Frankfurt, West Germany, Farbwerke Hoechst, 1964.
7. Haeussler A, Hajdu P: Methods of biological identification and results of studies on absorption, elimination, and metabolism. Internal report, Research Laboratories, Frankfurt, West Germany, Farbwerke Hoechst.
8. Wilson AF, Simmons DH: Diuretic action in hypochloremic dogs. Clin Res 14:158, 1966.
9. Hook JB, Williamson HE: Influence of probenecid and alterations and acid-base balance of the saluretic activity of furosemide. J Pharmacol Exp Ther 149:404-408, 1965.
10. Antoniou LD, et al: Sodium and calcium transport in the kidney. Clin Res 15:476, 1967.
11. Duarte CG: Effects of furosemide (F) and ethacrynic acid (ETA) on the renal clearance of phosphate (Cp), ultra-filterable calcium (CUf-Ca) and magnesium (CUfMg) Clin Res 15:357, 1967.
12. Duarte CG: Effects of ethacrynic acid and furosemide on urinary calcium, phosphate and magnesium. Metabolism 17:867-876, 1968.
13. Nielsen SP, Andersen O, Steven KE, Magnesium and calcium metabolism during prolonged furosemide (Lasix®) administration to normal rats. Acta Pharmacol Toxicol 27:469-479, 1969.
14.Reimold EW: The effect of furosemide on hypercalcemia due to dihydrotachysterol. Metabolism 21:593-598, 1972.

Package Insert Rev. 09-22

Manufactured by:

First Priority, Inc.
Elgin, IL 60123

Approved by FDA under ANADA # 200-373

Reorder #037750
Questions? (855) 724-3461

Distributed by:
Covetrus® North America
400 Metro Place North
Dublin, OH 43017
covetrus.com

Made in U.S.A.
AH-037750-L-03
Label/Carton REV: 0223